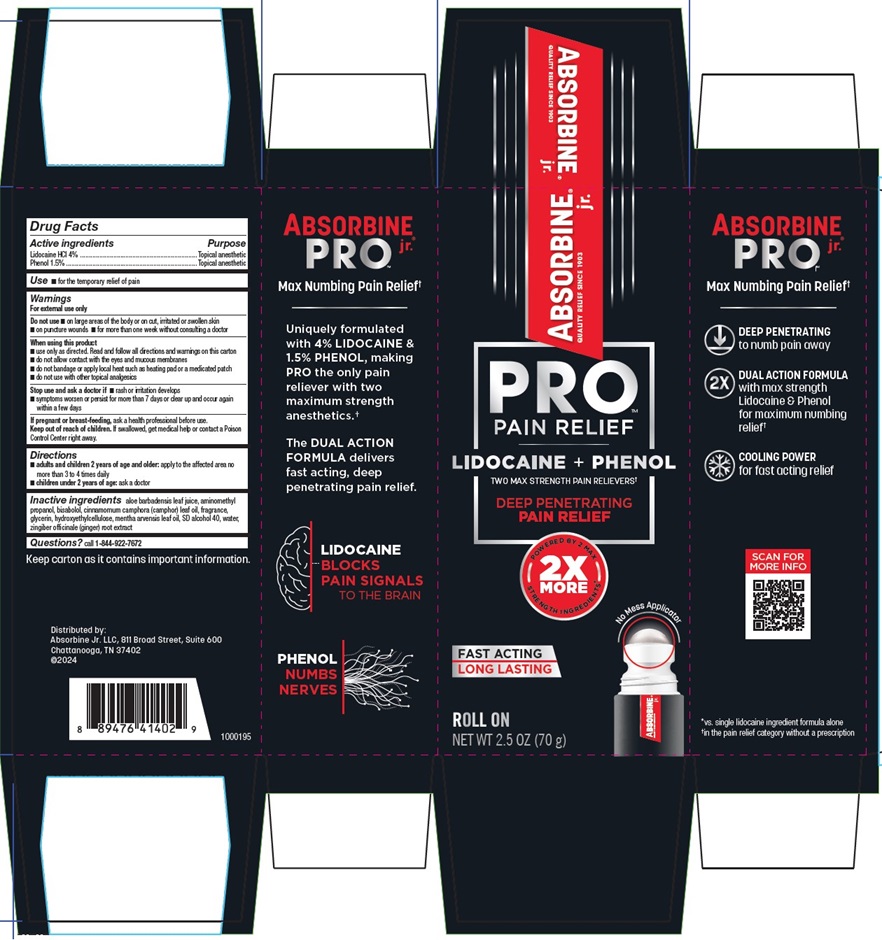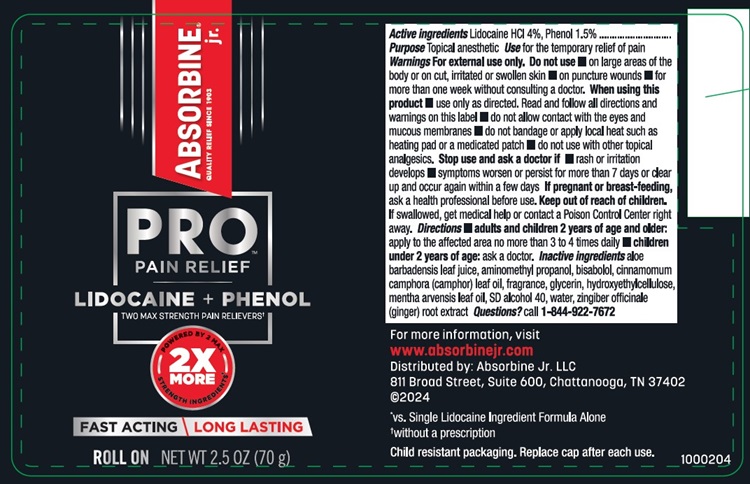 DRUG LABEL: Absorbine Jr Pro No Mess Roll-on
NDC: 69693-419 | Form: CREAM
Manufacturer: Clarion Brands, LLC
Category: otc | Type: HUMAN OTC DRUG LABEL
Date: 20251223

ACTIVE INGREDIENTS: LIDOCAINE 40 mg/1 g; PHENOL 15 mg/1 g
INACTIVE INGREDIENTS: ALOE VERA LEAF; AMINOMETHYLPROPANOL; LEVOMENOL; CAMPHOR LEAF OIL; GLYCERIN; HYDROXYETHYL CELLULOSE, UNSPECIFIED; ALCOHOL; MENTHA ARVENSIS LEAF OIL; WATER; GINGER

Absorbine Jr Pro No Mess Roll-on
Drug Facts

Active Ingredients

Lidocaine HCI 4%,
Phenol 1.5%

Purpose

Topical Analgesic

Use

for the temporary relief of pain

Warnings

Warnings For external use only.

Do not use

- on large areas of the body, or on cut, irritated or swollen skin
- on puncture wounds
- for more than one week without consulting a doctor.

When using this product

- use only as directed. Read and follow all directions and warnings on this label
- do not allow contact with the eyes and mucous membranes
- do not bandage tightly
- do not bandage or apply local heat such as heating pad or a medicated patch
- do not use with other topical analgesics.

Stop use and ask a doctor if

- rash or irritation develops
- symptoms worsen or persist for more than 7 days or clear up and occur again within a few days.

If pregnant or breast feeding,

ask a health professional before use.

Keep out of reach of children.

If swallowed, get medical help or contact a Poison Control Center right away.

Directions

- adults and children 2 years of age and older:apply to the affected area no more than 3 to 4 times daily
- children under 2 years of age;: ask a doctor

Inactive Ingredients

aloe barbadensis leaf juice, aminomethyl propanol, bisabolol, cinnamomum camphora (camphor) leaf oil, fragrance, glycerin, hydroxyethylcellulose, mentha arvensis leaf oil, SD alcohol 40, water, zingiber oficinale (ginger)

Questions?

call 1-844-922-7672

Principal Display Panel

ABSORBINE® jr.
QUALITY RELIEF SINCE 1903
PRO
PAIN RELIEF
LIDOCAINE + PHENOL
TWO MAX STRENGTH PAIN RELIEVERStDEEP PENETRATING
PAIN RELIEF
2X MORE
POWERED BY 2 MAX STRENGTH INGREDIENTS*
FAST ACTING - LONG LASTING
ROLL ON
NET WT 2.5 OZ (70 g)
ABSORBINE PRO™ jr.
Max Numbing Pain Relief†
Uniquely formulated
with 4% LIDOCAINE &
1.5% PHENOL, making
PRO the only pain
reliever with two
maximum strength
anesthetics.†
The DUAL ACTION
FORMULA delivers
fast acting, deep
penetrating pain relief.
LIDOCAINE
BLOCKS
PAIN SIGNALS
TO THE BRAIN
PHENOL
NUMBS
NERVES
Keep carton as it contains important information.
Distributed by:
Absorbine Jr. LLC, 811 Broad Street, Suite 600
Chattanooga, TN 37402
©2004
DEEP PENETRATING
to numb pain away
DUAL ACTION FORMULA
with max strength
Lidocaine & Phenol
for maximum numbing
relief†
COOLING POWER
for fast acting relief
*vs. single lidocaine ingredient formula alone
†in the pain relief category without a prescription
1000195

ABSORBINE® jr.
QUALITY RELIEF SINCE 1903
PRO
PAIN RELIEF
LIDOCAINE + PHENOL
TWO MAX STRENGTH PAIN RELIEVERS†
2X MORE
POWERED BY 2 MAX STRENGTH INGREDIENTS*
FAST ACTING - LONG LASTING
ROLL ON NET WT 2.5 OZ (70 g)

For more information, visit
www.Absorbine Jr.com
Distributed by: Absorbine Jr. LLC
811 Broad Street, Suite 600, Chattanooga, TN 37402
©2004
*vs. Single Lidocaine Ingredient Formula Alone
†without a prescription
Child resistant packaging. Replace cap after each use.
1000204